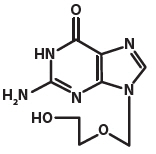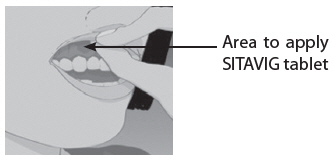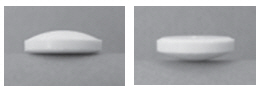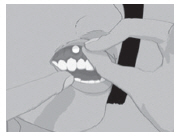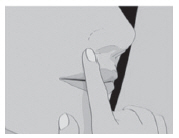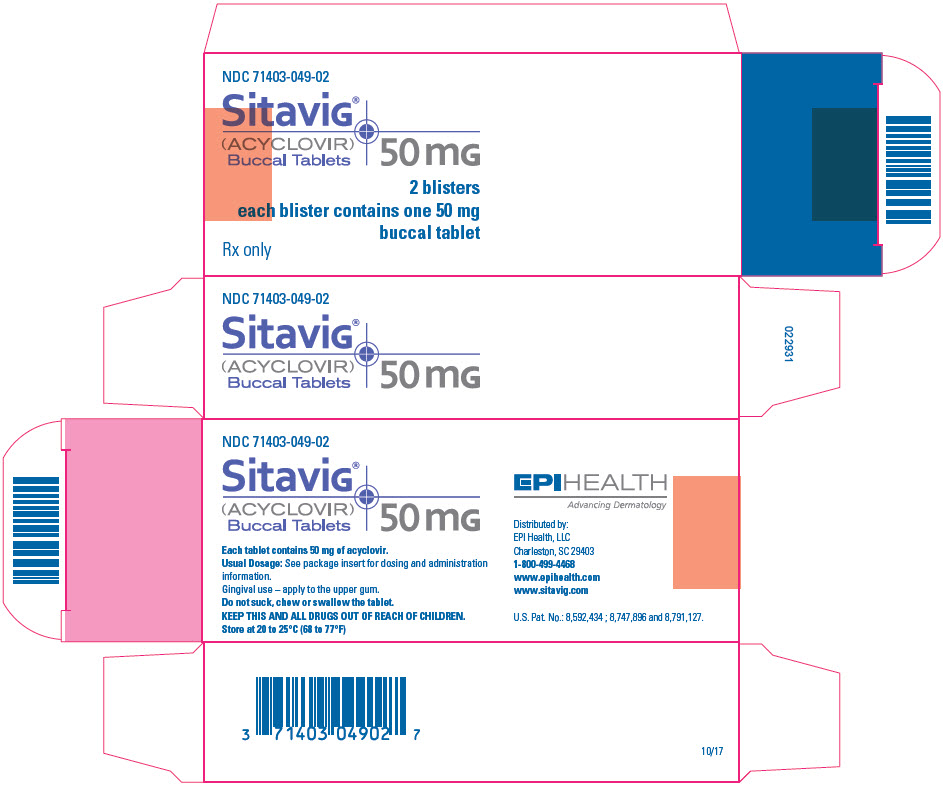 DRUG LABEL: Sitavig
NDC: 71403-049 | Form: TABLET, DELAYED RELEASE
Manufacturer: EPI Health, Inc
Category: prescription | Type: HUMAN PRESCRIPTION DRUG LABEL
Date: 20200611

ACTIVE INGREDIENTS: ACYCLOVIR 50 mg/1 1
INACTIVE INGREDIENTS: MICROCRYSTALLINE CELLULOSE; SODIUM LAURYL SULFATE; POVIDONE, UNSPECIFIED; WATER; HYPROMELLOSE 2208 (15000 MPA.S); MAGNESIUM STEARATE; SILICON DIOXIDE

HIGHLIGHTS OF PRESCRIBING INFORMATION

These highlights do not include all the information needed to use SITAVIG safely and effectively. See full prescribing information for SITAVIG.
SITAVIG (acyclovir) buccal tablets
Initial U.S. Approval: 1982

1 INDICATIONS AND USAGE

SITAVIG is a deoxynucleoside analogue of DNA polymerase inhibitor, indicated for the treatment of recurrent herpes labialis (cold sores) in immunocompetent adults. (1).

2 DOSAGE AND ADMINISTRATION

- Application of one SITAVIG 50 mg buccal tablet as a single dose to the upper gum (canine fossa) region (2.1).
- SITAVIG should be applied within one hour after the onset of prodromal symptoms and before the appearance of any signs of herpes labialis.
- Do not crush, chew, suck or swallow tablets (2.2).

3 DOSAGE FORMS AND STRENGTHS

50 mg buccal tablets (3).

4 CONTRAINDICATIONS

Known hypersensitivity to acyclovir, milk protein concentrate, or any other component of the product (4).

6 ADVERSE REACTIONS

Most common adverse reactions (≥1%) are: headache and application site pain (6.1).

To report SUSPECTED ADVERSE REACTIONS, contact EPI Health, LLC at 1-800-499-4468 or FDA at 1-800-FDA-1088 or www.fda.gov/medwatch.

7 DRUG INTERACTIONS

Due to the low dose and minimal systemic absorption of SITAVIG, drug interactions are unlikely (7)

FULL PRESCRIBING INFORMATION

1 INDICATIONS AND USAGE

SITAVIG is indicated for the treatment of recurrent herpes labialis (cold sores) in immunocompetent adults.

2 DOSAGE AND ADMINISTRATION

2.1 Basic Dosing Information

One SITAVIG 50 mg buccal tablet should be applied as a single dose to the upper gum region (canine fossa).

2.2 Administration Instructions

SITAVIG should be applied within one hour after the onset of prodromal symptoms and before the appearance of any signs of herpes labialis lesions. The tablet should be applied with a dry finger immediately after taking it out of the blister. The tablet should be placed to the upper gum just above the incisor tooth (canine fossa) and held in place with a slight pressure over the upper lip for 30 seconds to ensure adhesion. For comfort the rounded side should be placed to the upper gum, but either side of the tablet can be applied. Tablet should be applied on the same side of the mouth as the herpes labialis symptoms.

Once applied, SITAVIG stays in position and gradually dissolves during the day. [See Clinical Pharmacology (12.3)]. In addition,

- SITAVIG should not be crushed, chewed, sucked or swallowed.
- Food and drink can be taken normally when SITAVIG is in place. Avoid any situations which may interfere with adhesion of the tablet such as chewing gum, touching or pressing the tablet after placement, wearing upper dentures, and brushing teeth. If the teeth need to be cleaned while the tablet is in place, rinse the mouth gently. Drink plenty of liquids in the case of dry mouth.
- If SITAVIG does not adhere or falls off within the first 6 hours, the same tablet should be repositioned immediately. If the tablet cannot be repositioned, a new tablet should be placed.
- If SITAVIG is swallowed within the first 6 hours, the patient should drink a glass of water and a new tablet should be applied. [see Patient Counseling Information (17)].
- SITAVIG does not need to be reapplied if the tablet falls out or is swallowed after the first 6 hours.

3 DOSAGE FORMS AND STRENGTHS

SITAVIG is a buccal tablet containing 50 mg of acyclovir. SITAVIG tablets are round, off-white tablets, with a rounded side and a flat side. The tablets are marked with an "AL21" on the flat side.

4 CONTRAINDICATIONS

SITAVIG is contraindicated in patients with known hypersensitivity (e.g., anaphylaxis) to acyclovir, milk protein concentrate, or any other component of the product.

6 ADVERSE REACTIONS

6.1 Clinical Trial Experience

Because clinical trials are conducted under widely varying conditions, adverse reaction rates observed in the clinical trials of a drug cannot be directly compared to rates in the clinical trials of another drug and may not reflect the rates observed in clinical practice.

The overall safety of SITAVIG was assessed in 378 adult subjects having at least 4 herpes labialis episodes the previous year.

One randomized, double-blind, placebo controlled trial was conducted in patients with recurrent herpes labialis (cold sores). In this trial, 378 HSV infected subjects used SITAVIG as a single dose, and 397 subjects used placebo.

Selected treatment emergent adverse events without regard to causality and reported in at least 1% of patients can be seen in Table 1.

Table 1: Selected Treatment Emergent Adverse Events reported in at least 1% of patients
Event | SITAVIG N = 378 | Placebo N = 397
Nervous System Disorders
Headache | 3% | 3%
Dizziness | 1% | 1%
Lethargy | 1% | 0
Gastrointestinal system Disorders
Gingival Pain | 1% | 0.3%
Aphthous Stomatitis | 1% | 0
Administration Site Conditions
Application Site Pain | 1% | 1%
Application Site Irritation | 1% | 0
Skin and Subcutaneous Disorders
Erythema | 1% | 0.3%
Rash | 1% | 0.3%

The treatment emergent adverse events considered related to treatment that occurred in greater than or equal to 1% of patients included headache (1% SITAVIG vs. 2% placebo) and application site pain (1% both arms). There was no discontinuation of SITAVIG due to adverse drug reactions. Most treatment related adverse events were mild or moderate in severity. One report of headache from both treatment arms was classified as severe.

7 DRUG INTERACTIONS

No interaction studies have been performed with SITAVIG. Acyclovir is primarily eliminated unchanged in the urine via active tubular secretion. Drugs administered concomitantly that compete with tubular secretion may increase acyclovir plasma concentrations. However, due to the low dose and minimal systemic absorption of SITAVIG, systemic drug interactions are unlikely.

8 USE IN SPECIFIC POPULATIONS

8.1 Pregnancy

There are no available data on SITAVIG use in pregnant women. However, published observational studies over decades of use of acyclovir have not identified a drug-associated risk of major birth defects, miscarriage, or adverse maternal or fetal outcomes. Systemic exposure of acyclovir following buccal administration of SITAVIG is minimal [see Clinical Pharmacology (12.3)]. Animal reproduction studies have not been conducted with SITAVIG. Animal reproduction studies with systemic exposure of acyclovir have been conducted. Refer to oral and parental acyclovir prescribing information for additional details.

8.2 Lactation

There are no data on the presence of acyclovir in human milk following buccal administration. There are no data on the effects of acyclovir on the breastfed infant or milk production. Systemic exposure following buccal administration of acyclovir is minimal [see Clinical Pharmacology (12.3)]. The developmental and health benefits of breastfeeding should be considered along with the mother's clinical need for SITAVIG and any potential adverse effects on the breastfed child from SITAVIG or from the underlying maternal condition.

8.4 Pediatric Use

Safety and effectiveness of SITAVIG in pediatric patients have not been established. The ability of pediatric patients to comply with the application instructions has not been evaluated. Use in younger children is not recommended due to potential risk of choking.

8.5 Geriatric Use

Clinical studies of SITAVIG did not include sufficient numbers of subjects aged 65 and over to determine whether they respond differently from younger subjects.

8.6 Immunocompromised Patients

The safety of SITAVIG has not been studied in immunocompromised subjects.

10 OVERDOSAGE

Acyclovir absorption and systemic exposure following application of SITAVIG are minimal. Overdose is therefore unlikely [see Clinical Pharmacology (12.3)].

Symptomatic and supportive care is the basis for management.

11 DESCRIPTION

SITAVIG (acyclovir) buccal tablet is applied topically to the gum and releases acyclovir as the buccal tablet gradually dissolves [see Clinical Pharmacology (12.3)].

Acyclovir is a synthetic purine nucleoside analogue active against herpes viruses. The chemical name of acyclovir is 2-amino-1,9-dihydro-9-[(2-hydroxyethoxy)methyl]-6H-purin-6-one; it has a molecular formula of C8H11N5O3 and a molecular weight of 225. The structural formula is shown in Figure 1.

Figure 1: Structural Formula of Acyclovir

Acyclovir drug substance is a white or almost white crystalline powder.

SITAVIG contains 50 mg of acyclovir, USP and the following inactive ingredients: hypromellose, USP; milk protein concentrate; sodium lauryl sulfate, NF; magnesium stearate, NF; microcrystalline cellulose, NF; povidone, USP; colloidal silicon dioxide, NF.

12 CLINICAL PHARMACOLOGY

12.1 Mechanism of Action

Acyclovir is an antiviral drug active against α-herpesviruses [see Microbiology (12.4)].

12.3 Pharmacokinetics

Absorption and Distribution

Salivary

The pharmacokinetic parameters of acyclovir after a single dose of SITAVIG in the saliva and plasma of healthy volunteers are provided in Table 2.

Table 2: Pharmacokinetic (PK) Parameters of Acyclovir in Saliva and Plasma Following Application of a Single SITAVIG 50 mg Tablet in Healthy Volunteers (N = 12)
PK Parameters (N = 12) | Salivary Mean ±SD (Min - Max) | Plasma [Acyclovir plasma concentrations had a delayed appearance (undetectable at 5 hours) and were below the concentrations required for antiviral activity (range: 17.5 to 55.3 nanogram per mL).] Mean ±SD (Min - Max)
AUC0-24h (mcg∙h/mL) | 2900 ± 2400 (849 - 9450) | 0.225 + 0.132 (0.027-0.422)
Cmax (mcg/mL) | 440 ± 241 (149 – 959) | 0.028 + 0.010 (0.017-0.055)
Tmax (hour) [Median (Min – Max).] | 7.04 (3.07 – 18.05) | 12 (5-16)

In the Phase 3 study, the levels of acyclovir in saliva were measured within 24 hours of SITAVIG application in 56 patients with recurrent herpes labialis (mean value 88.1 micrograms per mL) and were within the range of those observed in the PK study in healthy volunteers.

In healthy volunteers, the median duration of buccal adhesion was 14 hours following application of a single SITAVIG 50 mg tablet.

Plasma

Plasma concentrations of acyclovir were measured in 12 healthy volunteers after a singledose application of SITAVIG 50 mg buccal tablet. Acyclovir concentrations had a delayed appearance (undetectable at 5 hours) and were below the concentrations required for antiviral activity (range: 17.5 to 55.3 nanogram per mL).

Metabolism and Excretion

Acyclovir is metabolized to 9-[(carboxymethoxy)methyl]guanine (CMMG) and 8-hydroxy-acyclovir (8-OH-ACV) by oxidation and hydroxylation, and is primarily excreted unchanged by the kidneys.

Food Effect

There was no formal food effect study conducted with SITAVIG; however, in clinical studies patients were allowed to eat and drink while taking SITAVIG.

12.4 Microbiology

Mechanism of Action

Acyclovir is a synthetic purine deoxynucleoside analogue with inhibitory activity against herpes simplex viruses type 1 (HSV-1) and type 2 (HSV-2) DNA polymerases. It inhibits HSV-1 and HSV-2 replication in cell culture and in vivo.

The inhibitory activity of acyclovir is selective due to its affinity for the enzyme thymidine kinase encoded by HSV. This viral enzyme converts acyclovir into acyclovir monophosphate, a deoxynucleotide analogue. The monophosphate is further converted into diphosphate by cellular guanylate kinase and into triphosphate by a number of cellular enzymes. In biochemical assays, acyclovir triphosphate inhibits replication of α-herpes viral DNA. This inhibition is accomplished in 3 ways: 1) competitive inhibition of viral DNA polymerase, 2) incorporation into and termination of the growing viral DNA chain, and 3) inactivation of the viral DNA polymerase.

Antiviral activity

The quantitative relationship between the susceptibility of herpes viruses to antivirals in cell culture and the clinical response to therapy has not been established in humans, and virus sensitivity testing has not been standardized. Sensitivity testing results, expressed as the concentration of drug required to inhibit by 50% the growth of virus in cell culture (EC50), vary greatly depending upon a number of factors. Using plaque-reduction assays on Vero cells, the EC50 values of acyclovir against herpes virus isolates ranged from 0.09 to 60 µM (0.02 to 13.5 µg/mL) for HSV-1 and from 0.04 to 44 µM (0.01 to 9.9 μg/mL) for HSV-2.

Resistance

In Cell Culture

Acyclovir-resistant HSV-1 and HSV-2 strains were isolated in cell culture. Acyclovirresistant HSV resulted from mutations in the viral thymidine kinase (TK; pUL23) and DNA polymerase (POL; pUL30) genes. Frameshifts were commonly isolated and result in premature truncation of the HSV TK product with consequent decreased susceptibility to acyclovir. Mutations in the viral TK gene may lead to complete loss of TK activity (TK negative), reduced levels of TK activity (TK partial), or alteration in the ability of viral TK to phosphorylate the drug without an equivalent loss in the ability to phosphorylate thymidine (TK altered). In cell culture the following resistance-associated substitutions in TK of HSV-1 and HSV-2 were observed (Table 3).

Table 3: Summary of Acyclovir (ACV) Resistance-associated Amino Acid Substitutions in Cell Culture
HSV-1 | TK | P5A, H7Q, L50V, G56V, G59A, G61A, K62N, T63A, E83K, P84S, D116N, P131S, R163H, A167V, P173L, Q185R, R216S, R220H, T245M, R281stop, T287M, M322K
HSV-2 | TK | L69P, C172R, T288M
HSV-1 | POL | D368A, Y557S, E597D, V621S, L702H, N815S, V817M,G841C
HSV-2 | POL | -

In HSV-Infected Patients

Clinical HSV-1 and HSV-2 isolates obtained from patients who failed treatment for their α-herpesvirus infections were evaluated for genotypic changes in the TK and POL genes and for phenotypic resistance to acyclovir (Table 4). HSV isolates with frameshift mutations and resistance-associated substitutions in TK and POL were identified. The listing of substitutions in the HSV TK and POL leading to decreased susceptibility to acyclovir is not all inclusive and additional changes will likely be identified in HSV variants isolated from patients who fail acyclovir-containing regimens. The possibility of viral resistance to acyclovir should be considered in patients who fail to respond or experience recurrent viral shedding during therapy.

Table 4: Summary of ACV Resistance-associated Amino Acid Substitutions Observed in Treated Patients
HSV-1 | TK | G6C, R32H, R41H, R51W, Y53C/D/H, Y53stop, D55N, G56D/S, P57H, H58N/R/Y, G59R, G61A, K62N, T63I, Q67stop, S74stop, Y80N, E83K, P84L, Y87H, W88R, R89Q/W, E95stop, T103P, Q104H, Q104stop, H105P, D116N, M121L/R, S123R, Q125H, M128L, G129D, I143V, A156V, D162A/H/N, R163G/H, L170P, Y172C, P173L, A174P, A175V, R176Q/W, R176stop, L178R, S181N, V187M, A189V, V192A, G200C/D/S, T201P, V204G, A207P, L208F/H, R216C/H, R220C/H, R221H, R222C/H, L227F, T245M/P, L249P, Q250Stop, C251G, R256W, E257K, Q261R, T287M, L288Stop, L291P/R, L297S, L315S, L327R, C336Y, Q342Stop, T354P, L364P, A365T
HSV-2 | TK | R34C, G39E, R51W, Y53N, G59P, G61W, S66P, A72S, D78N, P85S, A94V, N100H, I101S, Q105P, T131P, D137stop, F140L, L158P, S169P, R177W, S182N, M183I, V192M, G201D, R217H, R221C/H, Q222stop, R223H, Y239stop, R271V, P272S, D273R, T287M, C337Y
HSV-1 | POL | K532T, Q570R, L583V, A605V, A657T, D672N, V715G, A719T/V, S724N, F733C, E771Q, S775N, L778M, E798K, V813M, N815S, G841S, I890M, G901V, V958L, H1228D
HSV-2 | POL | E250Q, D307N, K533E, A606V, C625R, R628C, E678G, A724V, S725G, S729N, I731F, Q732R, M789K/T, V818A, N820S, Y823C, Q829R, T843A, M910T, D912N/V, A915V, F923L, T934A, R964H
Note: Many additional pathways to acyclovir resistance likely exist.

Cross-resistance

Cross-resistance has been observed among HSV isolates carrying frameshift mutations and resistance-associated substitutions, which confer reduced susceptibility to penciclovir (PCV), famciclovir (FCV), and foscarnet (FOS) [Table 5].

Table 5: Summary of Amino Acid Substitutions Conferring Cross-Resistance to PCV, FCV or FOS
Cross-resistant to PCV/FCV | HSV-1 TK | G6C, R32H, R51W, Y53C/H, H58N, G61A, S74Stop, E83K, P84L, T103P, Q104Stop, D116N, M121R, I143V, R163H, L170P, Y172C, A174P, R176Q/W, Q185R, A189V, G200D, L208H, R216C, R220H, R222C/H, T245M, Q250Stop, R256W, R281Stop, T287M, L315S, M322K, C336Y
Cross-resistant to PCV/FCV | HSV-1 POL | A657T, D672N, V715G, A719V, S724N, E798K, N815S, G841S
Cross-resistant to PCV/FCV | HSV-2 TK | G39E, R51W, Y53N, R177W, R221H, T288M
Cross-resistant to PCV/FCV | HSV-2 POL | K533E, A606V, C625R, R628C, S729N, Q732R, M789K/T, V818A, N820S, F923L, T934A
Cross-resistant to FOS | HSV-1 POL | D368A, A605V, D672N, L702H, V715G, A719T/V, S724N, L778M, E798K, V813M, N815S, V817M, G841C/S, I890M
Cross-resistant to FOS | HSV-2 POL | K533E, A606V, C625R, R628C, A724V, S725G, S729N, I731F, Q732R, M789K/T, V818A, Y823C D912V, F923L, T934A, R964H

13 NONCLINICAL TOXICOLOGY

13.1 Carcinogenesis, Mutagenesis, Impairment of Fertility

Systemic exposure following buccal administration of acyclovir is minimal. Results from previous studies of carcinogenesis, mutagenesis and fertility for acyclovir are not included in the full prescribing information for SITAVIG due to the minimal exposure that results from buccal administration. Information on these studies following systemic exposure is available in the full prescribing information for acyclovir products approved for oral and parenteral administration.

14 CLINICAL STUDIES

Study in Patients with Recurrent Herpes Labialis (cold sores)

The efficacy and safety of SITAVIG was evaluated in a randomized, double-blind, placebo-controlled, patient-initiated, multicenter trial comparing SITAVIG 50 mg administered as a single dose (n = 378) to placebo (n = 397) in patients with recurrent herpes labialis (cold sores). A total of 376 SITAVIG treated patients and 395 placebo treated patients were included in the Intent to Treat (ITT) efficacy population defined as all patients who took study treatment and who had a start date and time of treatment initiation recorded. The mean age was 41.0 years (range: 18-80 years) and the majority of patients were female (68.6%), and Caucasian (94.9%). All patients had at least 4 herpes episodes in the previous year of whom 68.4% had ≥ 5 episodes. Patients were instructed to initiate treatment within one hour after the onset of prodromal symptoms and before the appearance of any signs of herpes labialis lesions by applying the tablet to the buccal mucosa in the canine fossa. If the tablet was detached within the first 6 hours, subjects were instructed to reapply a tablet.

The mean and median durations of the recurrent herpes labialis episode (ITT population, n=771) were approximately half a day shorter in patients treated with SITAVIG compared with patients treated with placebo.

16 HOW SUPPLIED/STORAGE AND HANDLING

SITAVIG buccal tablets are supplied as off-white tablets containing 50 mg of acyclovir. SITAVIG tablets have a rounded side and a flat side and are imprinted with AL21 on one side. SITAVIG tablets are packaged in blisters of two tablets (NDC 71403-049-02).

STORAGE AND HANDLING

SITAVIG should be stored at 20 to 25°C (68 to 77°F) [see USP controlled room temperature]; excursions between 15 and 30°C (59-86°F) permitted at room temperature.

Protect from moisture and keep out of reach of children.

17 PATIENT COUNSELING INFORMATION

See FDA-approved patient labeling (Patient Information and Instructions for Use).

17.1 Instructions for Use

Read the Instructions for Use that comes with SITAVIG before you start using it. Talk to your doctor or pharmacist if you have any questions.

Important:
SITAVIG should be applied to the area of the upper gum above the incisor tooth.
SITAVIG tablets should not be crushed, sucked, chewed or swallowed.

If it comes out before 6 hours have gone by, reapply it. If this does not work then a new tablet should be applied.
It should not be applied to the inside of the lip or cheek.

- Tablet should be applied on the same side of the mouth as the herpes labialis symptoms.
- Do not remove SITAVIG if it sticks to your upper gum. If SITAVIG does not stick or falls off of your upper gum within the first 6 hours that you apply it, place it back onto your upper gum. If it still does not stick, replace it with a new SITAVIG tablet.
- Do not re-apply SITAVIG if it falls out or you swallow it after it has been in place 6 hours or longer.
- If you swallow SITAVIG within the first 6 hours of applying it, drink a glass of water and place a new SITAVIG tablet onto your upper gum.

17.2 Adverse Reactions

Patients may experience adverse reactions including headache, and application site pain.

Patient Information
SITAVIG (SIT-a-vig)
(acyclovir) buccal tablets

What is SITAVIG?

- SITAVIG is a prescription medicine used to treat cold sores (herpes labialis) in adults with normal immune systems.
- It is not known if SITAVIG is safe and effective in children.

Who should not use SITAVIG?
Do not use SITAVIG if you are allergic to:

- acyclovir or any of the ingredients in SITAVIG. See the end of this leaflet for a complete list of ingredients in SITAVIG.
- milk protein concentrate

Before using SITAVIG, tell your healthcare provider about all of your medical conditions, including if you:

- are pregnant or plan to become pregnant. It is not known if SITAVIG will harm your unborn baby.
- are breastfeeding or plan to breastfeed. It is not known if SITAVIG passes into your breast milk. Talk to your healthcare provider about the best way to feed your baby during treatment with SITAVIG.
- Tell your healthcare provider about all the medicines you take, including prescription or over-the-counter medicines, vitamins, and herbal supplements.

How should I use SITAVIG?
See the detailed Instructions for Use for information about how to use SITAVIG.

- Use SITAVIG exactly as your healthcare provider tells you to use it.
- Use SITAVIG within 1 hour after you have the first symptom of a cold sore, such as itching, redness, burning, or tingling, and before a cold sore appears.
- You may eat and drink while using SITAVIG.
- Do not crush, chew, suck, or swallow SITAVIG tablets.
- SITAVIG will slowly dissolve over time while in your mouth and should be left in place.
- Gently rinse your mouth with water to clean your teeth while SITAVIG is in place.
- Drink more liquids if your mouth becomes dry while using SITAVIG.

What should I avoid while using SITAVIG?
You should avoid activities that may prevent SITAVIG from sticking to your gum, including: touching or pressing SITAVIG after you apply it, wearing upper dentures, chewing gum, and brushing your teeth during the treatment day.

What are the possible side effects of SITAVIG?
The most common side effects of SITAVIG include: headache and pain where SITAVIG is applied.
These are not all the possible side effects of SITAVIG. Call your doctor for medical advice about side effects. You may report side effects to FDA at 1-800-FDA-1088.

How should I store SITAVIG?

- Store SITAVIG between 68°F to 77°F (20°C to 25°C). Keep SITAVIG tablets dry.

Keep SITAVIG and all medicines out of the reach of children.

General information about the safe and effective use of SITAVIG
Medicines are sometimes prescribed for purposes other than those listed in a Patient Information leaflet. Do not use SITAVIG for a condition for which it was not prescribed. Do not give SITAVIG to other people, even if they have the same symptoms that you have. It may harm them. You can ask your pharmacist or healthcare provider for information about SITAVIG that is written for health professionals.

What are the ingredients in SITAVIG?
Active ingredient: acyclovir
Inactive ingredients: hypromellose, milk protein concentrate, sodium lauryl sulfate, magnesium stearate, microcrystalline cellulose, povidone, colloidal silicon dioxide.
Manufactured By: Farméa, 10 rue Bouché Thomas, ZAC d'orgemont, 49 000 Angers - France
For more information call 1-800-499-4468.

This Patient Information has been approved by the U.S. Food and Drug Administration.

Revised: 12/2019

Instructions for Use
SITAVIG (SIT-a-vig)
(acyclovir) buccal tablets

Read the Instructions for Use that comes with SITAVIG before you start using it. Talk to your healthcare provider or pharmacist if you have any questions.

Important:

- SITAVIG should be applied within 1 hour after you have the first symptom of a cold sore, such as itching, redness, burning, or tingling, and before a cold sore appears.
- SITAVIG should be applied on the same side of your mouth as the cold sore symptoms.
- SITAVIG should be applied to your upper gum, just above your incisor tooth.
- SITAVIG should not be applied to the inside of your lip or your cheek.
- If SITAVIG does not stick to your upper gum or falls off of your upper gum within the first 6 hours after you apply it, the same tablet should be placed back onto your upper gum right away. If this SITAVIG tablet does not stay in place, apply another SITAVIG tablet to your upper gum.
- Do not re-apply SITAVIG if it falls out or you swallow it after it has been in place 6 hours or longer.
- If you swallow SITAVIG within the first 6 hours of applying it, drink a glass of water and place a new SITAVIG tablet onto your upper gum.

How to apply SITAVIG:

Step 1: | Before you apply SITAVIG, find the area on your upper gum, just above either the left or the right incisor. The incisor tooth is the tooth just to the right or left of your two front teeth (See Figure A). This is where you should apply SITAVIG.
 | Figure A
Step 2: | Peel back the cover of the blister pack. Take 1 SITAVIG out of the blister pack. When removed from the blister pack, SITAVIG must be used right away. SITAVIG is round on one side and flat on the other side (See Figure B).
 | Figure B
Step 3: | Place the flat side of SITAVIG on your dry fingertip. Apply the round side of SITAVIG to your upper gum (See Figure C). The flat side will be facing the inside of your lip.
 | Figure C
Step 4: | Hold SITAVIG in place by applying a slight pressure with your finger on the outside of your upper lip, over the area where SITAVIG is placed, for 30 seconds. This will help SITAVIG stick to your gum (See Figure D).
 | Figure D
Step 5: | Leave the SITAVIG tablet in place until it dissolves.

This Instructions for Use has been approved by the U.S. Food and Drug Administration.

Manufactured By:
Farméa
10 rue Bouché Thomas
ZAC d'orgemont
49 000 Angers - France

Distributed By:
EPI Health, LLC
Charleston, SC 29403
1-800-499-4468
www.epihealth.com
www.sitavig.com

U.S. Pat. No.: 8,592,434 ; 8,747,896 and 8,791,127.

©EPI Health, LLC

Revision date: 12/2019

SIT-PI-0220

023220

PRINCIPAL DISPLAY PANEL - 50 mg Tablet Blister Pack Carton

NDC 71403-049-02

Sitavig®

(ACYCLOVIR)
Buccal Tablets

50 mg

2 blisters
each blister contains one 50 mg
buccal tablet

Rx only